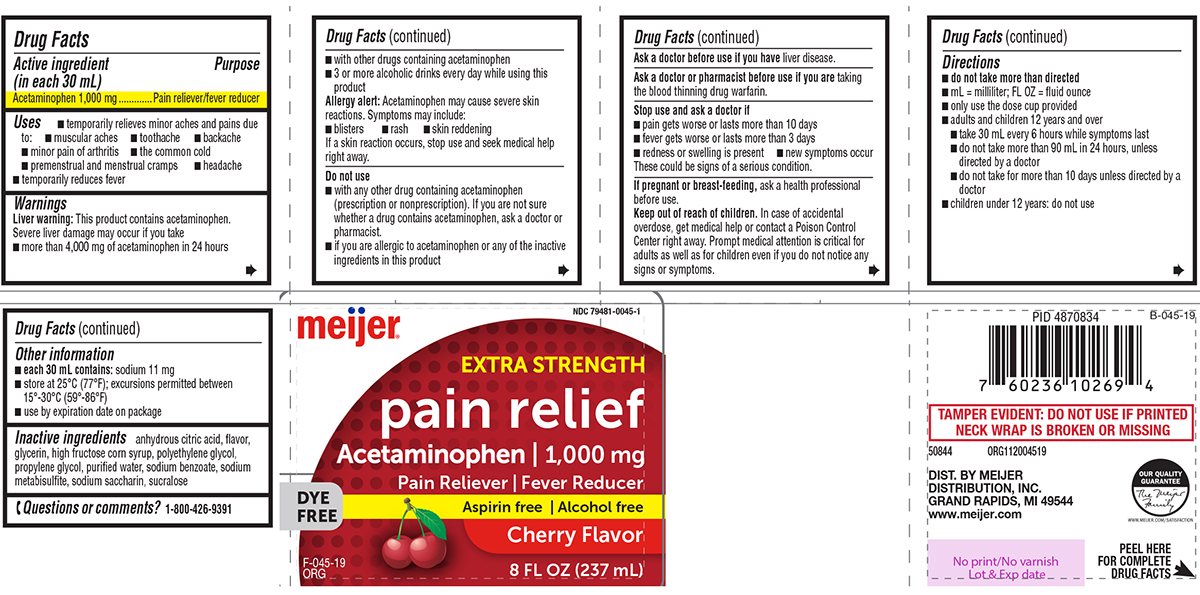 DRUG LABEL: pain relief
NDC: 79481-0045 | Form: SOLUTION
Manufacturer: Meijer Distribution, Inc.
Category: otc | Type: HUMAN OTC DRUG LABEL
Date: 20251115

ACTIVE INGREDIENTS: ACETAMINOPHEN 1000 mg/30 mL
INACTIVE INGREDIENTS: ANHYDROUS CITRIC ACID; GLYCERIN; HIGH FRUCTOSE CORN SYRUP; POLYETHYLENE GLYCOL, UNSPECIFIED; PROPYLENE GLYCOL; WATER; SODIUM BENZOATE; SODIUM METABISULFITE; SACCHARIN SODIUM; SUCRALOSE

Meijer 44-045

Active ingredient (in each 30 mL)

Acetaminophen 1,000 mg

Purpose

Pain reliever/fever reducer

Uses

- temporarily relieves minor aches and pains due to:
  - muscular aches
  - toothache
  - backache
  - minor pain of arthritis
  - the common cold
  - premenstrual and menstrual cramps
  - headache
- temporarily reduces fever

Warnings

Liver warning: This product contains acetaminophen. Severe liver damage may occur if you take

- more than 4,000 mg of acetaminophen in 24 hours
- with other drugs containing acetaminophen
- 3 or more alcoholic drinks every day while using this product

Allergy alert: Acetaminophen may cause severe skin reactions. Symptoms may include:

- blisters
- rash
- skin reddening

If a skin reaction occurs, stop use and seek medical help right away.

Do not use

- with any other drug containing acetaminophen (prescription or nonprescription). If you are not sure whether a drug contains acetaminophen, ask a doctor or pharmacist.
- if you are allergic to acetaminophen or any of the inactive ingredients in this product

Ask a doctor before use if you have

liver disease.

Ask a doctor or pharmacist before use if you are

taking the blood thinning drug warfarin.

Stop use and ask a doctor if

- pain gets worse or lasts more than 10 days
- fever gets worse or lasts more than 3 days
- redness or swelling is present
- new symptoms occur

These could be signs of a serious condition.

If pregnant or breast-feeding,

ask a health professional before use.

Keep out of reach of children.

In case of accidental overdose, get medical help or contact a Poison Control Center right away. Prompt medical attention is critical for adults as well as for children even if you do not notice any signs or symptoms.

Directions

- do not take more than directed
- mL = milliliter; FL OZ = fluid ounce
- only use the dose cup provided
- adults and children 12 years and over
  - take 30 mL every 6 hours while symptoms last
  - do not take more than 90 mL in 24 hours, unless directed by a doctor
  - do not take for more than 10 days unless directed by a doctor
- children under 12 years: do not use

Other information

- each 30 mL contains: sodium 11 mg
- store at 25°C (77°F); excursions permitted between 15°-30°C (59°-86°F)
- use by expiration date on package

Inactive ingredients

anhydrous citric acid, flavor, glycerin, high fructose corn syrup, polyethylene glycol, propylene glycol, purified water, sodium benzoate, sodium metabisulfite, sodium saccharin, sucralose

Questions or comments?

1-800-426-9391

Principal display panel

meijer®

NDC 79481-0045-1

EXTRA STRENGTH
pain relief
Acetaminophen I 1,000 mg
Pain Reliever I Fever Reducer

DYE FREE

Aspirin free I Alcohol free
Cherry Flavor

8 FL OZ (237 mL)

F-045-19
ORG

TAMPER EVIDENT: DO NOT USE IF PRINTED NECK WRAP IS BROKEN OR MISSING

50844 ORG112004519

DIST. BY MEIJER
DISTRIBUTION, INC.
GRAND RAPIDS, MI 49544
www.meijer.com

OUR QUALITY
GUARANTEE
The Meijer
Family
WWW.MEIJER.COM/SATISFACTION

Meijer 44-045